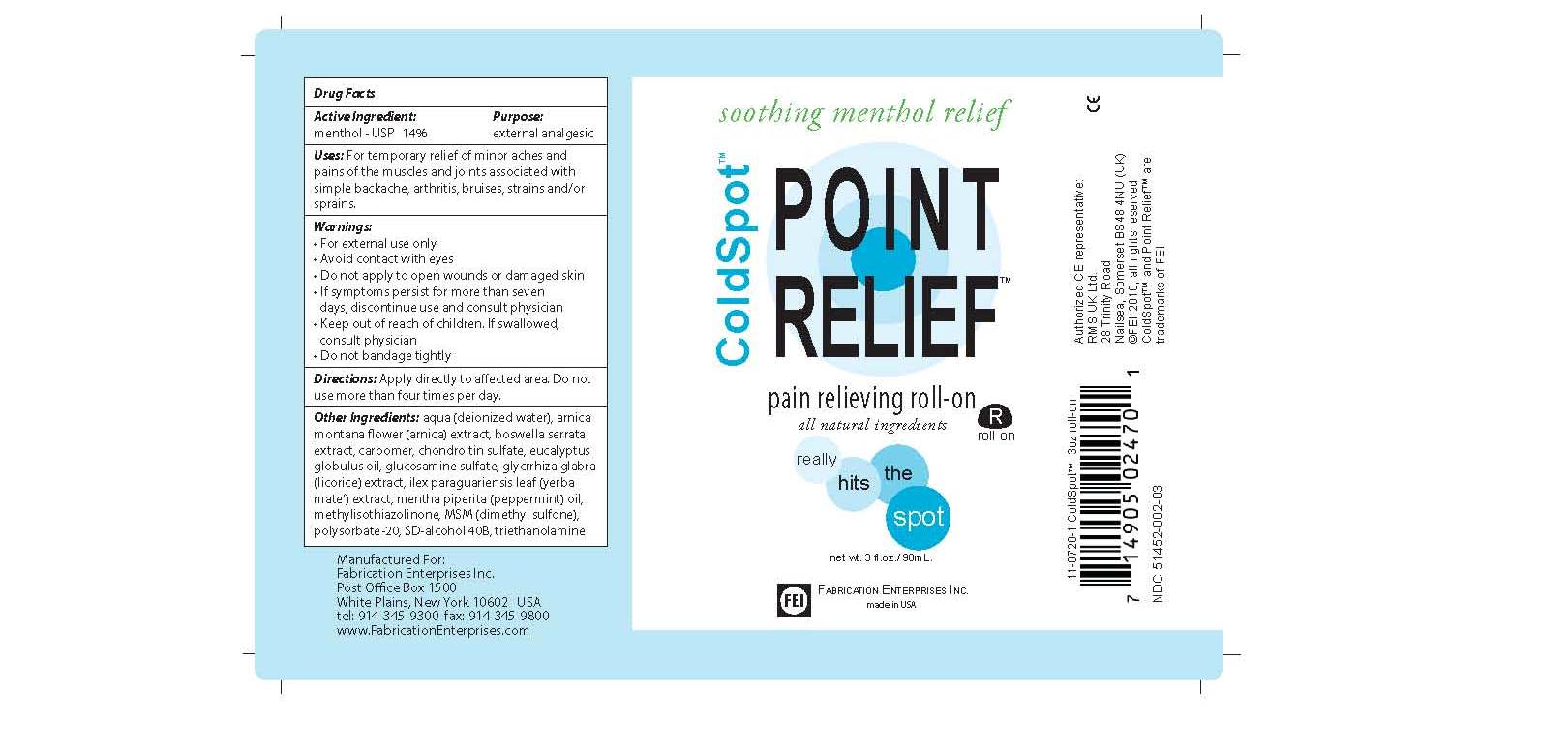 DRUG LABEL: Cold Spot
NDC: 51452-002 | Form: OINTMENT
Manufacturer: Fabrication Enterprises
Category: otc | Type: HUMAN OTC DRUG LABEL
Date: 20101005

ACTIVE INGREDIENTS: MENTHOL 13 mL/90 mL
INACTIVE INGREDIENTS: WATER; ARNICA CORDIFOLIA FLOWER; CHONDROITIN SULFATE (BOVINE); EUCALYPTUS GLOBULUS LEAF; GLUCOSAMINE SULFATE; ILEX PARAGUARIENSIS LEAF; CARBOMER 1342; peppermint oil; DIMETHYL SULFONE; POLYSORBATE 20; ALCOHOL

Cold Spot Point Relief Pain relieving Roll On - 3 oz.

Active Ingredients: Menthol

INACTIVE INGREDIENT

Inactive Ingredients: deionized water, arnica, chondroitin sulfate, citirc acid, euclayptus oil, glucosamine sulfate, ilex paraguariesis leaf, isopropyl alcohol, peppermint oil, dimethyl sulfone, polysorbate-20, SD alcohol 40B.

Keep out of reach of children. If swallowed consult physician

WARNINGS

Warnings Section: For external use only, avoid contact with eyes, do not apply to open wounds or damaged skin, if symptoms persist for more than seven days discontinue use and consult physician, keep out of reach of children and if swallowed consult physician, do not bandage tightly.

PURPOSE

pain relief

INDICATIONS AND USAGE

Use: For temporary relief of minor aches and pains of the muscles and joints associated with simple backache, arthritis, bruises, strains and/or sprains.

DOSAGE AND ADMINISTRATION

Apply directly to effected area. Do not use more than four times per day.

PACKAGE LABEL

ColdSpot Point Relief Pain Relieving spray, all natural ingredients.